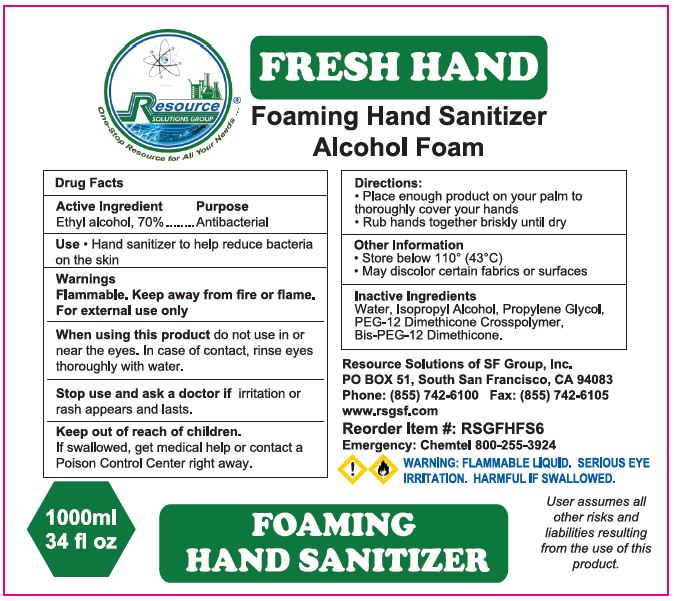 DRUG LABEL: FRESH HAND FOAMING HAND SANITIZER ALCOHOL FOAM
NDC: 70415-203 | Form: SOLUTION
Manufacturer: CWGC LA Inc.
Category: otc | Type: HUMAN OTC DRUG LABEL
Date: 20230921

ACTIVE INGREDIENTS: ALCOHOL 70 mL/100 mL
INACTIVE INGREDIENTS: WATER; ISOPROPYL ALCOHOL; PROPYLENE GLYCOL; PEG-12 DIMETHICONE (300 CST); BIS-PEG-12 DIMETHICONE (70 MPA.S)

CWGC (as PLD) - Resource Solutions 70% Foaming Hand Sanitizer Alcohol Foam (70415-203)

Active ingredient

Ethyl Alcohol 70 %

Purpose

Antibacterial

PURPOSE

ANTIBACTERIAL

Uses

- Hand sanitizer to help reduce bacteria on the skin.

WARNINGS

Flammable. Keep away from fire or flame.

For external use only.

When using this product do not use in or near the eyes. In case of contact, rinse eyes thoroughly with water.

Stop use and ask a doctor if irritation or rash appears and lasts.

When using this product

- avoid contact with eyes. In case of eye contact, flush with water

Keep out of reach of children.

If swallowed, get medical help or contact a Poison Control Center right away.

Keep out of reach of children.

If swallowed, get medical help or contact a Poison Control Center right away.

DIRECTIONS

- Place enough product on your palm to thoroughly cover your hands
- Rub hands together briskly until dry

Inactive ingredients

Water, Isopropyl Alcohol, Propylene Glycol, PEG-12 Dimethicone Crosspolymer, BIS-PEG-12 Dimethicone.